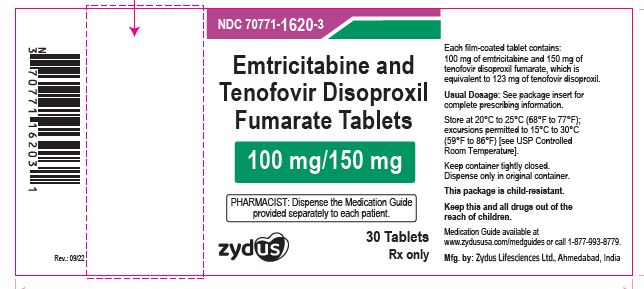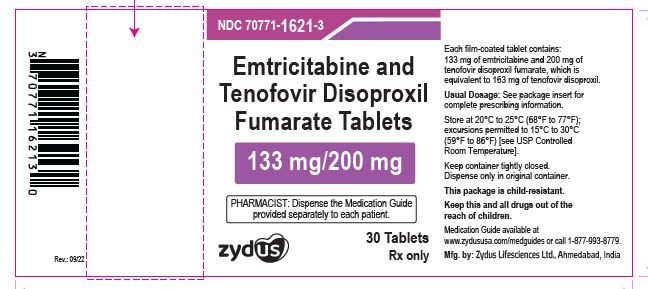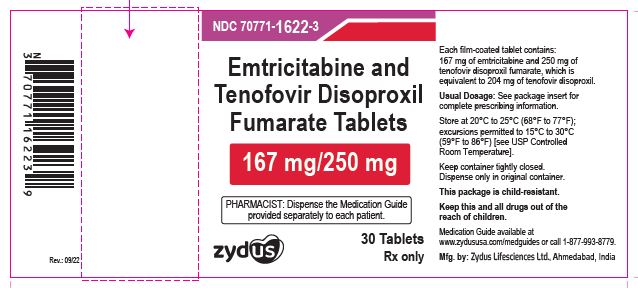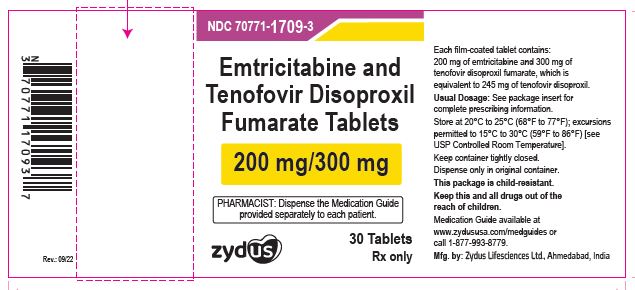 DRUG LABEL: Emtricitabine and tenofovir disoproxil fumarate
NDC: 70771-1620 | Form: TABLET, FILM COATED
Manufacturer: Zydus Lifesciences Limited
Category: prescription | Type: HUMAN PRESCRIPTION DRUG LABEL
Date: 20241128

ACTIVE INGREDIENTS: EMTRICITABINE 100 mg/1 1; TENOFOVIR DISOPROXIL FUMARATE 150 mg/1 1
INACTIVE INGREDIENTS: CROSCARMELLOSE SODIUM; GLYCERYL MONOCAPRYLOCAPRATE; HYPROMELLOSE 2910 (5 MPA.S); KAOLIN; LACTOSE MONOHYDRATE; MICROCRYSTALLINE CELLULOSE; STARCH, CORN; SODIUM LAURYL SULFATE; SODIUM STEARYL FUMARATE; TITANIUM DIOXIDE; POLYVINYL ALCOHOL, UNSPECIFIED

Emtricitabine and Tenofovir Disoproxil Fumarate Tablets

PACKAGE LABEL.PRINCIPAL DISPLAY PANEL

NDC 70771-1620-3

Emtricitabine and Tenofovir Disoproxil Fumarate Tablets, 100 mg/150 mg

Rx Only

30 tablets

NDC 70771-1621-3

Emtricitabine and Tenofovir Disoproxil Fumarate Tablets, 133 mg/200 mg

Rx Only

30 tablets

NDC 70771-1622-3

Emtricitabine and Tenofovir Disoproxil Fumarate Tablets, 167 mg/250 mg

Rx Only

30 tablets

NDC 70771-1709-3

Emtricitabine and Tenofovir Disoproxil Fumarate Tablets, 200 mg/300 mg

Rx Only

30 tablets